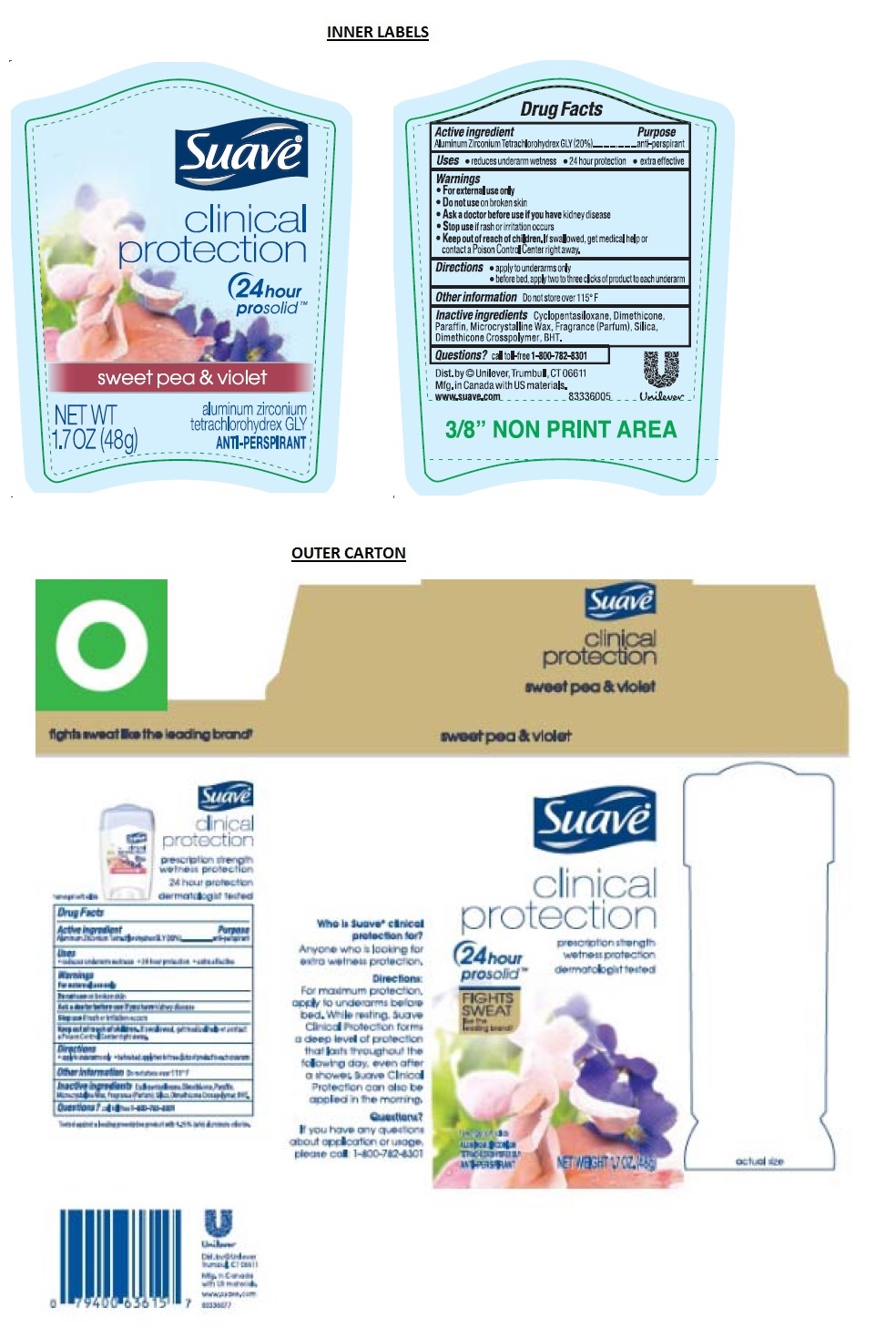 DRUG LABEL: Suave
NDC: 64942-1458 | Form: STICK
Manufacturer: Conopco Inc. d/b/a Unilever
Category: otc | Type: HUMAN OTC DRUG LABEL
Date: 20210813

ACTIVE INGREDIENTS: ALUMINUM ZIRCONIUM TETRACHLOROHYDREX GLY 20 g/100 g
INACTIVE INGREDIENTS: CYCLOMETHICONE 5; DIMETHICONE; PARAFFIN; MICROCRYSTALLINE WAX; SILICON DIOXIDE; BUTYLATED HYDROXYTOLUENE

Suave - Clinical Protection Sweet Pea and Violet Anti-Perspirant

Active ingredient

Aluminum Zirconium Tetrachlorohydrex GLY(20%)

Purpose

anti-perspirant

Uses

• reduces underarm wetness • 24 hour protection • extra effective

Warnings

• For external use only

• Do not use on broken skin

• Ask a doctor before using if you have kidney disease

• Stop use if rash or irritation occurs

• Keep out of reach of children. If swallowed, get medical help or contact a Poison Control Center right away.

Directions

• apply to underarms only
• before bed, apply two to three clicks of product to each underarm

Inactive ingredients

Cyclopentasiloxane, Dimethicone, Paraffin, Microcrystalline Wax, Fragrance (Parfum), Silica, Dimethicone Crosspolymer, BHT

Questions?

call toll-free 1-800-782-8301